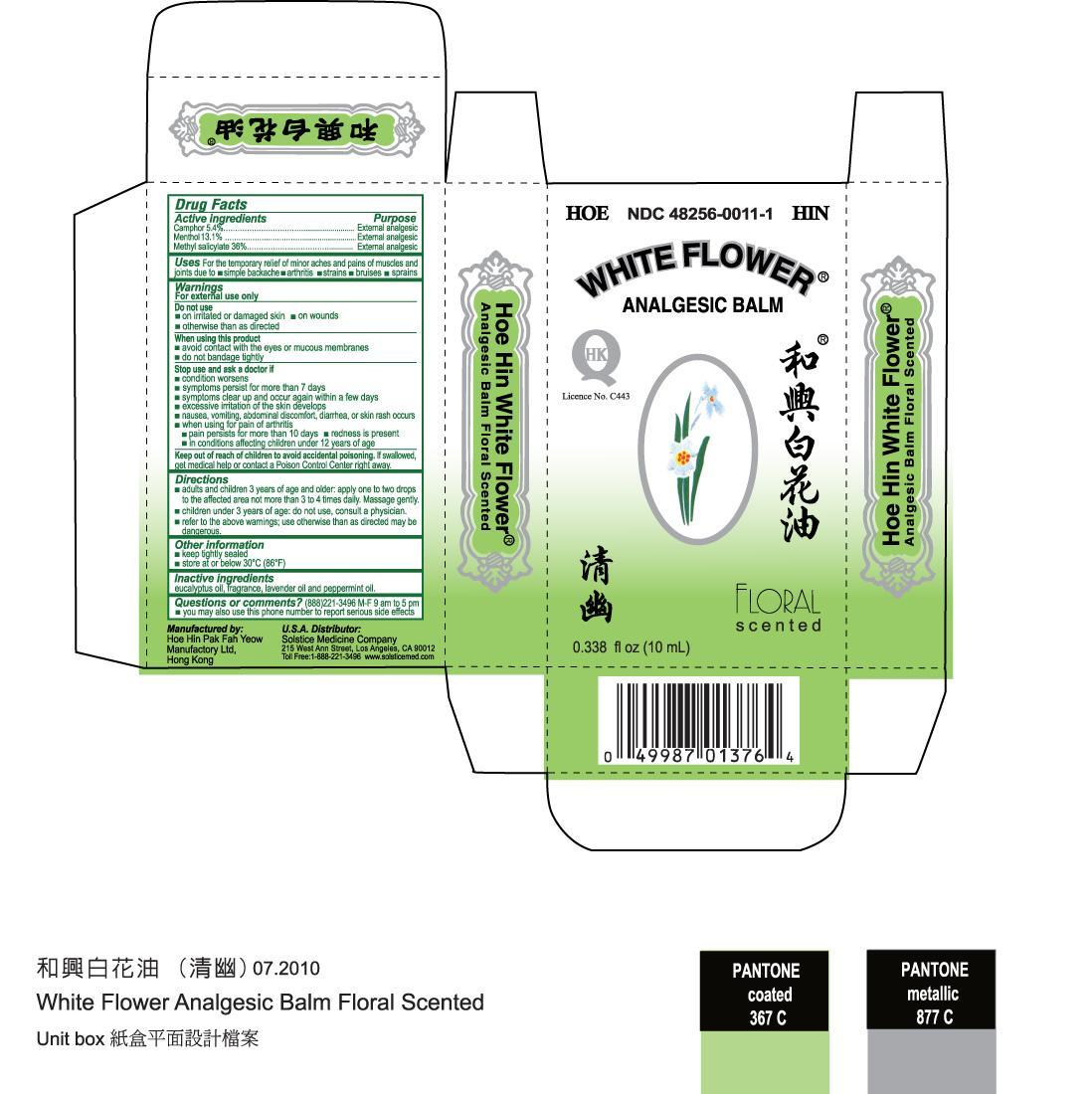 DRUG LABEL: WHITE FLOWER ANALGESIC BALM FLORAL SCENTED
NDC: 48256-0011 | Form: OIL
Manufacturer: HOE HIN PAK FAH YEOW MANUFACTORY LTD
Category: otc | Type: HUMAN OTC DRUG LABEL
Date: 20231002

ACTIVE INGREDIENTS: CAMPHOR (SYNTHETIC) 5.4 g/100 mL; MENTHOL 13 g/100 mL; METHYL SALICYLATE 35.8 g/100 mL
INACTIVE INGREDIENTS: EUCALYPTUS OIL; LAVENDER OIL; PEPPERMINT OIL

DRUG FACTS

Active ingredients

Camphor 5.4%

Menthol 13.1%

Methyl salicylate 36%

Purpose

External analgesic

Do not use

- on irritated or damaged skin
- on wounds
- otherwise than as directed

When using this product

- avoid contact with the eyes or mucous membranes
- do not bandage tightly

Stop use and ask a doctor if

- condition worsens
- symptoms persist for more than 7 days
- symptoms clear up and occur again within a few days
- excessive irritation of the skin develops
- nausea, vomiting, abdominal discomfort, diarrhea, or skin rash occurs
- when using for pain of arthritis:
-
  - pain persists for more than 10 days
  - redness is present
  - in conditions affecting children under 12 years of age

Keep out of reach of children to avoid accidental poisoning.

If swallowed, get medical help or contact a Poison Control Center right away.

Directions

- adults and children 3 years of age and older: apply one to two drops to the affected area not more than 3 to 4 times daily. Massage gently.
- children under 3 years of age and pregnant women: do not use, consult a physician
- refer to the above warnings; use otherwise than as directed may be dangerous

Other information

- keep tightly sealed
- store at or below 30º C (86º F), away from direct sunlight

INACTIVE INGREDIENT

Inactive ingredients eucalyptus oil, fragrance, lavender oil, and peppermint oil.

Questions or comments? (888) 221-3496 M-F 9 am to 5 pm

- you may also use this phone number to report serious side effects

INDICATIONS AND USAGE

Uses For the temporary relief of minor aches and pains of muscles and joints due to:

- simple backache
- arthritis
- strains
- bruises
- sprains

Warnings

For external use only

PACKAGE LABEL

WHITE FLOWER ANALGESIC BALM FLORAL SCENTED NDC-48256-0011-1 0.338 fl oz (10 mL)